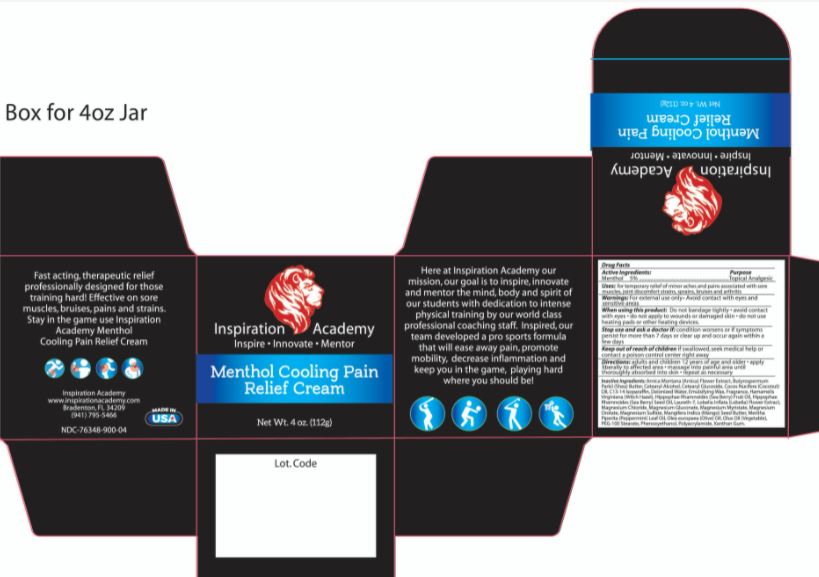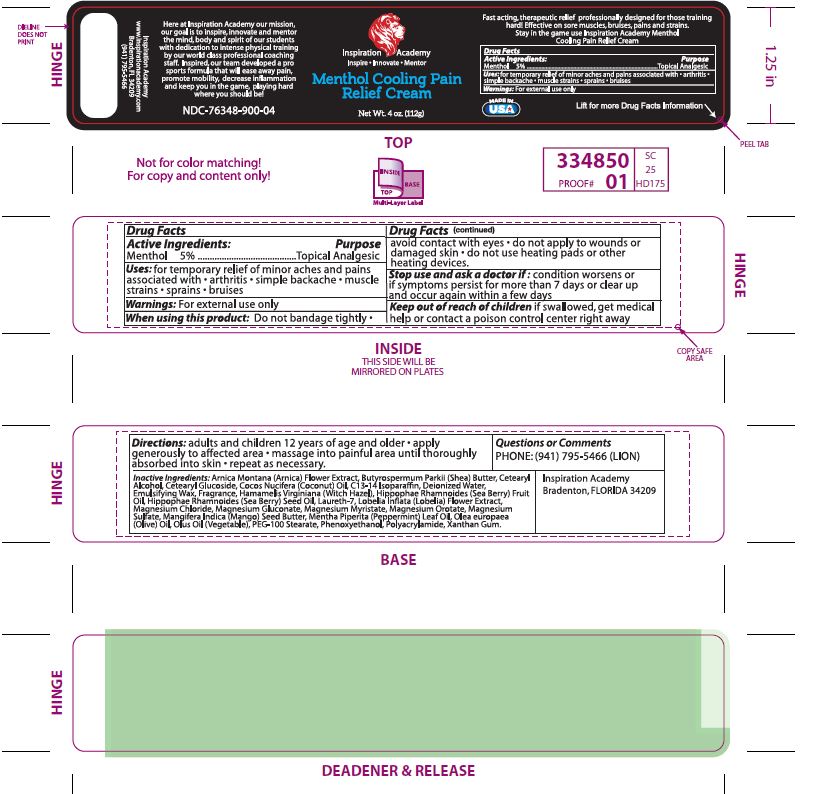 DRUG LABEL: Inspiration Academy Menthol Cooling Pain Cream
NDC: 76348-900 | Form: CREAM
Manufacturer: Renu Laboratories, Inc.
Category: otc | Type: HUMAN OTC DRUG LABEL
Date: 20220103

ACTIVE INGREDIENTS: MENTHOL 5.6 g/112 g
INACTIVE INGREDIENTS: ARNICA MONTANA FLOWER; HIPPOPHAE RHAMNOIDES SEED OIL; PEG-100 STEARATE; HIPPOPHAE RHAMNOIDES FRUIT OIL; SHEA BUTTER; CETOSTEARYL ALCOHOL; C13-14 ISOPARAFFIN; WATER; WHITE WAX; WITCH HAZEL; CETEARYL GLUCOSIDE; COCONUT OIL; LAURETH-7; LOBELIA INFLATA; MAGNESIUM CHLORIDE; MAGNESIUM GLUCONATE; MAGNESIUM MYRISTATE; PHENOXYETHANOL; PEPPERMINT OIL; CORN OIL; OLIVE OIL; XANTHAN GUM; MAGNESIUM OROTATE; MAGNESIUM SULFATE, UNSPECIFIED; MANGIFERA INDICA SEED BUTTER; POLYACRYLAMIDE (10000 MW)

Inspiration Academy Menthol Cooling Pain Relief Cream

Active Ingredients:

Menthol 5%

Keep out of reach of children

If swallowed, get medical help or contact a poison control center right away.

Purpose

Topical Analgesic

Questions or Comments

PHONE: (941) 795-5466 (LION)

Stop use and ask a doctor if

condition worsens or if symptoms persist for more than seven days or clear up and occur again within a few days

When using this product:

- Do not bandage tightly
- avoid contact with eye
- do not apply to wounds or damaged skin
- do not use heating pads or other heating devices.

Directions:

adults and children 12 years of age and older

- apply generously to affected area
- massage into painful area until thoroughly absorbed into skin
- repeat as necessary

INACTIVE INGREDIENT

Arnica Montana (Arnica) Flower Extract, Butyrospermum Parkii (Shea) Butter,

Cetearyl Alcohol, Cetearyl Glucoside, Cocos Nucifera (Coconut) Oil, C13-14 Isoparaffin, Deionized Water,

Emulsifying Wax, Fragrance, Hamamelis Virginiana (Witch Hazel), Hippophae Rhamnoides (Sea Berry) Fruit and Seed Oil,

Laureth-7, Lobelia Inflata (Lobelia) Flower Extract, Magnesium Chloride, Magnesium Gluconate, Magnesium Myristate, Magnesium Orotate, Magnesium Sulfate, Mangifera Indica (Mango) Seed Butter, Mentha Piperita (Peppermint) Leaf Oil, Olea europaea (Olive) Oil,

Olus Oil (Vegetable), PEG-100 Stearate, Phenoxyethanol, Polyacrylamide, Xanthan Gum.

Uses:

for temporary relief of minor aches and pains associated with sore muscles, joint discomfort, strains, sprains, bruises and arthritis.

WARNINGS

For external use only

RECENT MAJOR CHANGES

Dosage and Administration

The only change is the effective date

Indications and Usage

The only change is the effective date

PACKAGE LABEL AND BOX ART